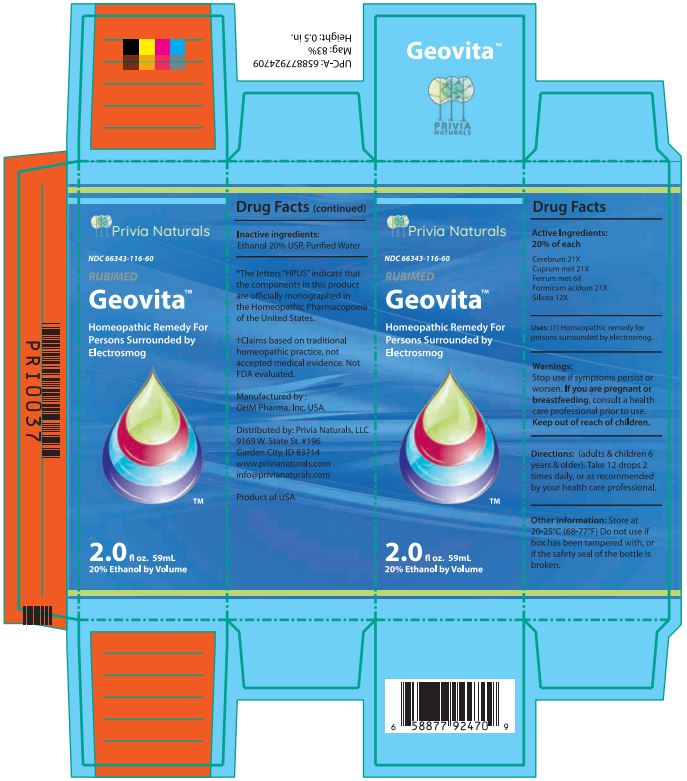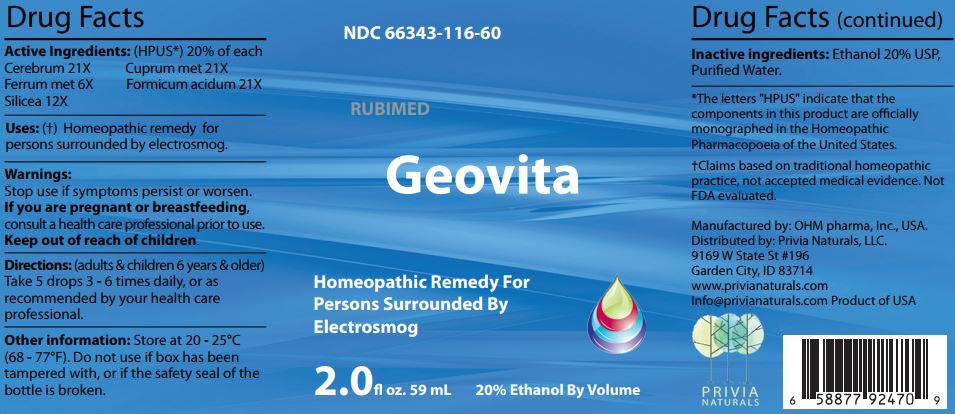 DRUG LABEL: Geovita
NDC: 66343-116 | Form: LIQUID
Manufacturer: RUBIMED AG
Category: homeopathic | Type: HUMAN OTC DRUG LABEL
Date: 20241129

ACTIVE INGREDIENTS: SUS SCROFA CEREBRUM 21 [hp_X]/60 mL; COPPER 21 [hp_X]/60 mL; IRON 6 [hp_X]/60 mL; FORMIC ACID 21 [hp_X]/60 mL; SILICON DIOXIDE 12 [hp_X]/60 mL
INACTIVE INGREDIENTS: ALCOHOL; WATER

Geovita

Drug Facts Active Ingredients: (HPUS*) 20% of each

Cerebrum 21X Cuprum met 21X
Ferrum met 6X Formicum acidum 21X
Silicea 12X

*The letters "HPUS" indicate that the components in this product are officially monographed in the Homeopathic Pharmacopoeia of the United States. †Claims based on traditional homeopathic practice, not accepted medical evidence. Not FDA evaluated.

INDICATIONS AND USAGE

Uses: (†) Homeopathic remedy for persons surrounded by electrosmog.

Warnings:

Stop use if symptoms persist or worsen.

If you are pregnant or breastfeeding,consult a healthcare professional prior to use.

Keep out of reach of children.

DOSAGE AND ADMINISTRATION

Directions: (adults & children 6 years & older)

Take 5 drops 3-6 times daily, or as

recommended by your health care

professional.

Other information: Store at 20 - 25°C

(68 - 77°F.) Do not use if box has been

tampered with, or if the safety seal of the

bottle is broken.

Inactive ingredients:Ethanol 20% USP,

Purified Water.

QUESTIONS

Manufactured by: OHM pharma, Inc, USA.

Distributed by: Privia Naturals, LLC.

9169 W State St #196

Garden City, ID 83714

www.privianaturals.com

Info@privianaturals.com Product of USA.

PACKAGE LABEL

NDC 66343-116-60

RUBIMED

Geovita

Homeopathic Remedy For

Persons Surrounded by

Electrosmog

2.0 fl oz. 59mL 20% Ethanol

PURPOSE

Homeopathic Remedy For

Persons Surrounded By

Electrosmog